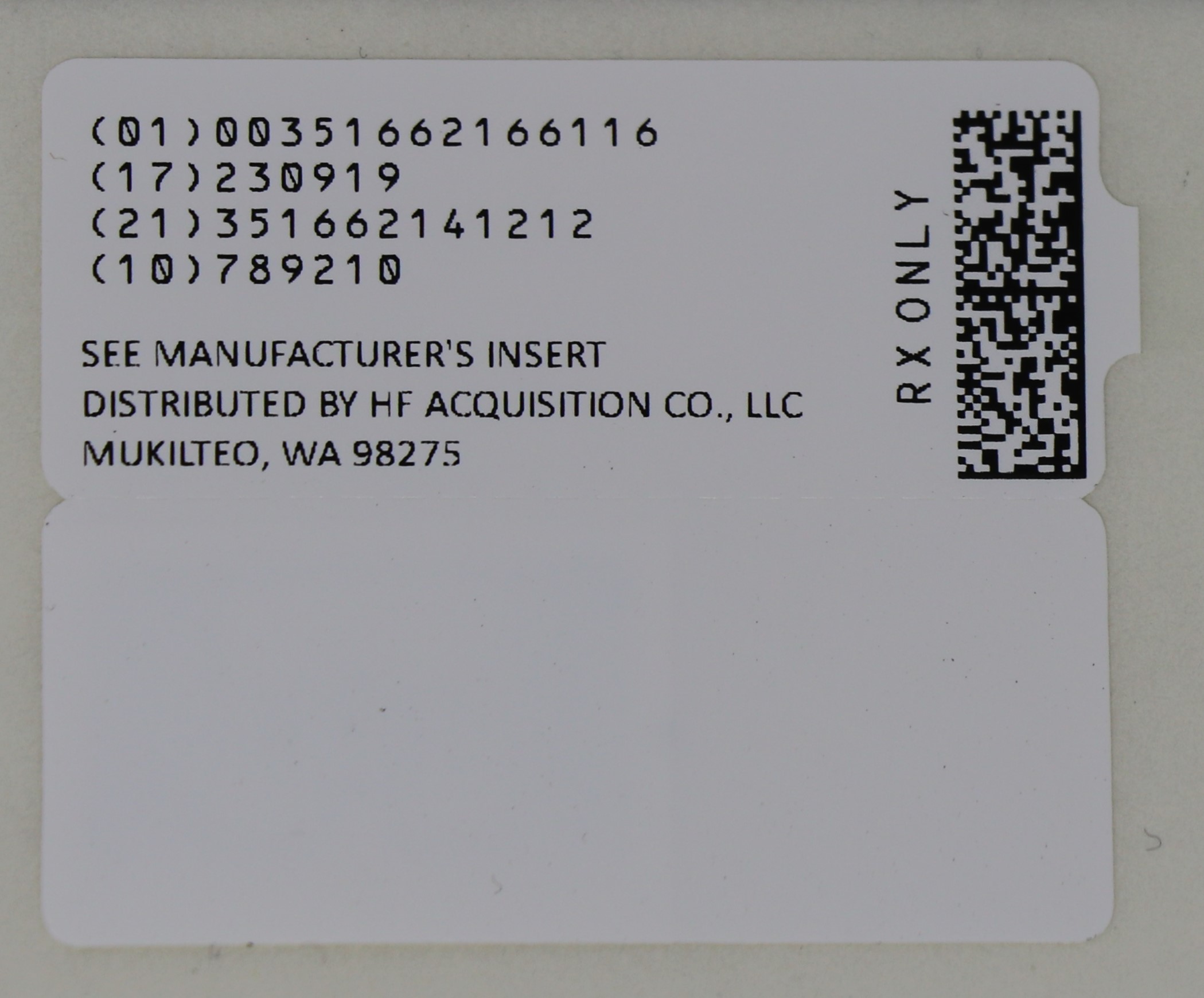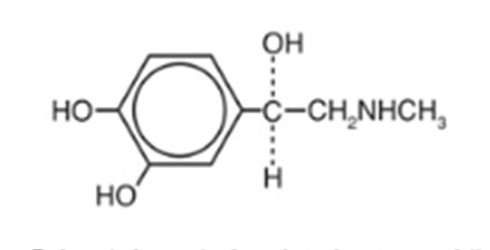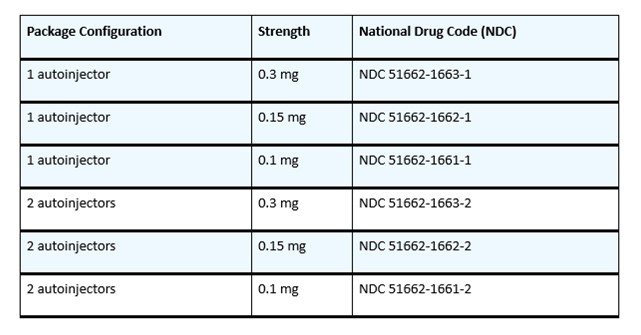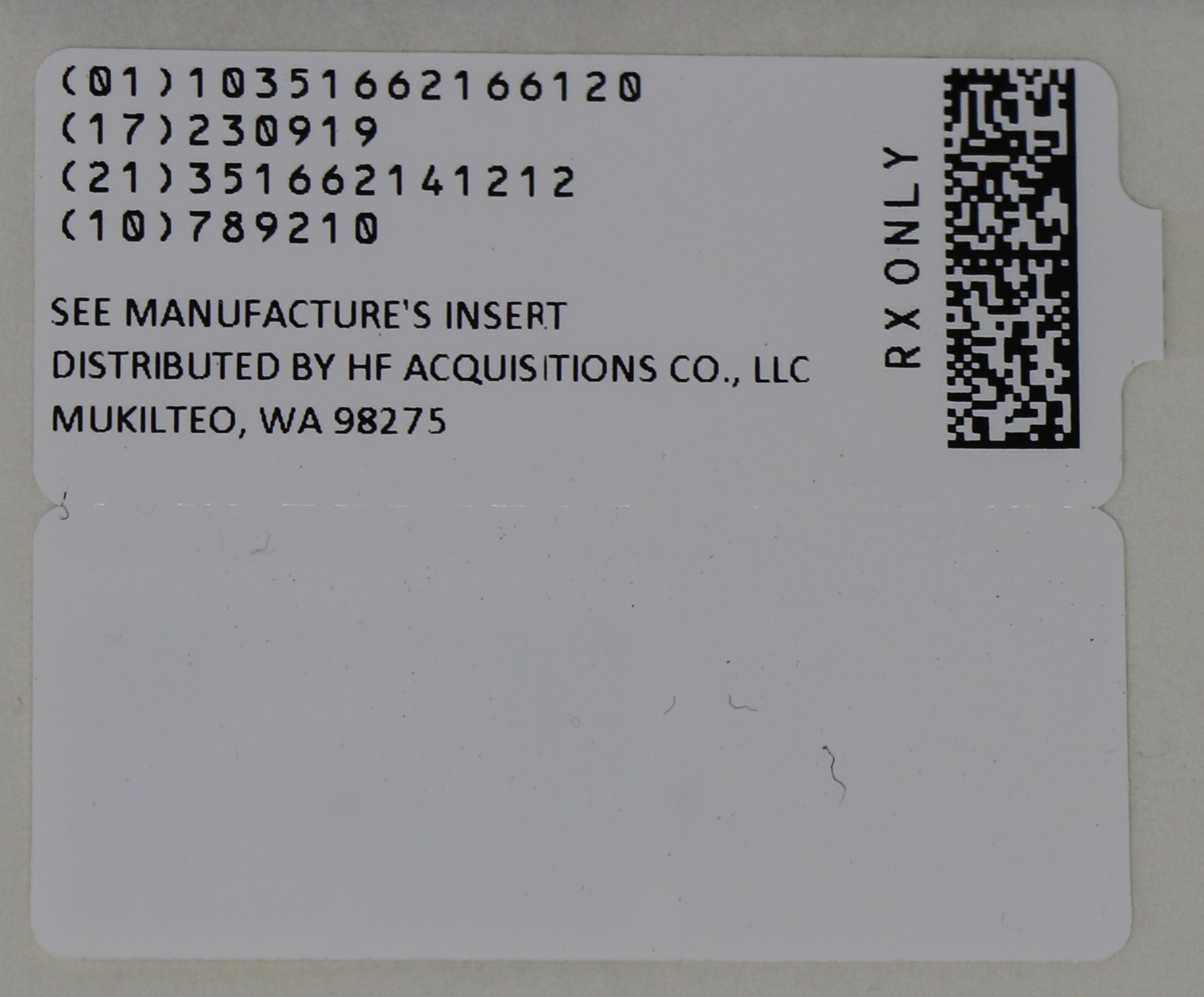 DRUG LABEL: AUVI-Q
NDC: 51662-1661 | Form: INJECTION, SOLUTION
Manufacturer: HF Acquisition Co LLC, DBA HealthFirst
Category: prescription | Type: HUMAN PRESCRIPTION DRUG LABEL
Date: 20250507

ACTIVE INGREDIENTS: EPINEPHRINE 0.1 mg/0.1 mL
INACTIVE INGREDIENTS: SODIUM CHLORIDE 0.78 mg/0.1 mL; WATER; SODIUM BISULFITE 0.15 mg/0.1 mL; HYDROCHLORIC ACID

HIGHLIGHTS OF PRESCRIBING INFORMATION

These highlights do not include all the information needed to use AUVI-Q® safely and effectively. See full prescribing information for AUVI-Q.
AUVI-Q® (epinephrine injection, USP),
for intramuscular or subcutaneous use
Initial U.S. Approval: 1939

INDICATIONS AND USAGE

AUVI-Q is a non-selective alpha and beta-adrenergic receptor agonist indicated in the emergency treatment of allergic reactions (Type I) including anaphylaxis. (1)

DOSAGE AND ADMINISTRATION

Patients greater than or equal to 30 kg (66 lbs): AUVI-Q 0.3 mg (2)
Patients 15 to 30 kg (33 to 66 lbs): AUVI-Q 0.15 mg (2)
Patients 7.5 to 15 kg (16.5 to 33 lbs): AUVI-Q 0.1 mg (2)

Inject AUVI-Q intramuscularly or subcutaneously into the anterolateral aspect of the thigh, through clothing if necessary. Each device is a single-dose injection. (2)

DOSAGE FORMS AND STRENGTHS

Injection:

0.3 mg: 0.3 mg/0.3 mL epinephrine injection, USP, pre-filled autoinjector (3)
0.15 mg: 0.15 mg/0.15 mL epinephrine injection, USP, pre-filled autoinjector (3)
0.1 mg: 0.1 mg/0.1 mL epinephrine injection, USP, pre-filled autoinjector (3)

CONTRAINDICATIONS

None. (4)

WARNINGS AND PRECAUTIONS

In conjunction with use, seek immediate medical or hospital care. (5.1)
Do not inject intravenously, into buttock, or into digits, hands, or feet. (5.2)
To minimize the risk of injection-related injury, instruct caregivers to hold the child’s leg firmly in place and limit movement prior to and during injection when administering to young children or infants. (5.2)
Rare cases of serious skin and soft tissue infections have been reported following epinephrine injection. Advise patients to seek medical care if they develop signs or symptoms of infection at the epinephrine injection site. (5.3)
The presence of a sulfite in this product should not deter use. (5.4)
Administer with caution in patients with heart disease; may aggravate angina pectoris or produce ventricular arrhythmias. (5.5)

ADVERSE REACTIONS

Adverse reactions to epinephrine include anxiety, apprehensiveness, restlessness, tremor, weakness, dizziness, sweating, palpitations, pallor, nausea and vomiting, headache, and/or respiratory difficulties. (6)

To report SUSPECTED ADVERSE REACTIONS, contact kaleo, Inc. at 1-877-302-8847 or FDA at 1-800-FDA-1088 or www.fda.gov/medwatch.

DRUG INTERACTIONS

Cardiac glycosides or diuretics: observe for development of cardiac arrhythmias. (7)
Tricyclic antidepressants, monoamine oxidase inhibitors, levothyroxine sodium, and certain antihistamines: potentiate effects of epinephrine. (7)
Beta-adrenergic blocking drugs: antagonize cardiostimulating and bronchodilating effects of epinephrine. (7)
Alpha-adrenergic blocking drugs: antagonize vasoconstricting and hypertensive effects of epinephrine. (7)
Ergot alkaloids: may reverse the pressor effects of epinephrine. (7)

USE IN SPECIFIC POPULATIONS

Elderly patients may be at greater risk of developing adverse reactions. (5.5, 8.5)

See 17 for PATIENT COUNSELING INFORMATION and FDA-approved patient labeling.

Revised: 2/2024

TABLE OF CONTENTS

FULL PRESCRIBING INFORMATION: CONTENTS*
1 INDICATIONS AND USAGE
2 DOSAGE AND ADMINISTRATION
3 DOSAGE FORMS AND STRENGTHS
4 CONTRAINDICATIONS
5 WARNINGS AND PRECAUTIONS
5.1 Emergency Treatment
5.2 Injection-Related Complications
5.3 Serious Infections at the Injection Site
5.4 Allergic Reactions Associated with Sulfite
5.5 Disease Interactions
6 ADVERSE REACTIONS
7 DRUG INTERACTIONS
7.1 Drugs Increasing Risk of Cardiac Arrhythmias
7.2 Drugs Potentiating Effects of Epinephrine
7.3 Drugs Antagonizing Effects of Epinephrine
8 USE IN SPECIFIC POPULATIONS
8.1 Pregnancy
8.2 Lactation
8.4 Pediatric Use
8.5 Geriatric Use
10 OVERDOSAGE
11 DESCRIPTION
12 CLINICAL PHARMACOLOGY
12.1 Mechanism of Action
12.2 Pharmacodynamics
13 NONCLINICAL TOXICOLOGY
13.1 Carcinogenesis, Mutagenesis, Impairment of Fertility
16 HOW SUPPLIED/STORAGE AND HANDLING
17 PATIENT COUNSELING INFORMATION

*
Sections or subsections omitted from the full prescribing information are not listed.

1 INDICATIONS AND USAGE

AUVI-Q® is indicated in the emergency treatment of allergic reactions (Type I) including anaphylaxis to stinging insects (e.g., order Hymenoptera, which include bees, wasps, hornets, yellow jackets and fire ants) and biting insects (e.g., triatoma, mosquitoes), allergen immunotherapy, foods, drugs, diagnostic testing substances (e.g., radiocontrast media) and other allergens, as well as idiopathic anaphylaxis or exercise-induced anaphylaxis.

AUVI-Q is intended for immediate administration in patients who are determined to be at increased risk for anaphylaxis, including individuals with a history of anaphylactic reactions.

Anaphylactic reactions may occur within minutes after exposure and consist of flushing, apprehension, syncope, tachycardia, thready or unobtainable pulse associated with a fall in blood pressure, convulsions, vomiting, diarrhea and abdominal cramps, involuntary voiding, wheezing, dyspnea due to laryngeal spasm, pruritus, rashes, urticaria or angioedema.

AUVI-Q is intended for immediate self-administration as emergency supportive therapy only and is not a substitute for immediate medical care.

2 DOSAGE & ADMINISTRATION

Selection of the appropriate dosage strength (AUVI-Q 0.3 mg, AUVI-Q 0.15 mg or AUVI-Q 0.1 mg) is determined according to patient body weight.

Patients greater than or equal to 30 kg (approximately 66 pounds or more): AUVI-Q 0.3 mg
Patients 15 to 30 kg (33 to 66 pounds): AUVI-Q 0.15 mg
Patients 7.5 to 15 kg (16.5 to 33 pounds): AUVI-Q 0.1 mg

Inject AUVI-Q intramuscularly or subcutaneously into the anterolateral aspect of the thigh, through clothing if necessary. Instruct caregivers of young children and infants who are prescribed AUVI-Q and who may be uncooperative and kick or move during an injection to hold the child’s leg firmly in place and limit movement prior to and during an injection [see Warnings and Precautions (5.2)].

Each AUVI-Q contains a single dose of epinephrine for single-dose injection. Since the doses of epinephrine delivered from AUVI-Q are fixed, consider using other forms of injectable epinephrine if doses lower than 0.1 mg are deemed necessary.

The prescriber should carefully assess each patient to determine the most appropriate dose of epinephrine, recognizing the life-threatening nature of the reactions for which this drug is indicated. With severe persistent anaphylaxis, repeat injections with an additional AUVI-Q may be necessary. More than two sequential doses of epinephrine should only be administered under direct medical supervision [see Warnings and Precautions (5.1)].

The epinephrine solution in the viewing window of AUVI-Q should be inspected visually for particulate matter and discoloration. Epinephrine is light sensitive and should be stored in the outer case provided to protect it from light [see How Supplied/ Storage and Handling (16)].

3 DOSAGE FORMS & STRENGTHS

Injection:

0.3 mg/0.3 mL epinephrine injection, USP, pre-filled autoinjector
0.15 mg/0.15 mL epinephrine injection, USP, pre-filled autoinjector
0.1 mg/0.1 mL epinephrine injection, USP, pre-filled autoinjector

4 CONTRAINDICATIONS

NONE

5 WARNINGS AND PRECAUTIONS

5.1 Emergency Treatment

AUVI-Q is not intended as a substitute for immediate medical care. In conjunction with the administration of epinephrine, the patient should seek immediate medical or hospital care. More than two sequential doses of epinephrine should only be administered under direct medical supervision [see Indications and Usage (1), Dosage and Administration (2) and Patient Counseling Information (17)].

5.2 Injection-Related Complications

AUVI-Q should ONLY be injected into the anterolateral aspect of the thigh [see Dosage and Administration (2) and Patient Counseling Information (17)].

Do not inject intravenously. Large doses or accidental intravenous injection of epinephrine may result in cerebral hemorrhage due to sharp rise in blood pressure. Rapidly acting vasodilators can counteract the marked pressor effects of epinephrine if there is such inadvertent administration.
Do not inject into buttock. Injection into the buttock may not provide effective treatment of anaphylaxis. Advise the patient to go immediately to the nearest emergency room for further treatment of anaphylaxis. Additionally, injection into the buttock has been associated with Clostridial infections (gas gangrene). Cleansing with alcohol does not kill bacterial spores, and therefore, does not lower this risk.
Do not inject into digits, hands or feet. Since epinephrine is a strong vasoconstrictor, accidental injection into the digits, hands or feet may result in loss of blood flow to the affected area. Advise the patient to go immediately to the nearest emergency room and to inform the healthcare provider in the emergency room of the location of the accidental injection. Treatment of such inadvertent administration should consist of vasodilation, in addition to further appropriate treatment of anaphylaxis [see Adverse Reactions (6)].
Hold leg firmly during injection. To minimize the risk of injection-related injury when administering AUVI-Q to young children or infants, instruct caregivers to hold the child’s leg firmly in place and limit movement prior to and during injection.

5.3 Serious Infections at the Injection Site

Rare cases of serious skin and soft tissue infections, including necrotizing fasciitis and myonecrosis caused by Clostridia (gas gangrene), have been reported at the injection site following epinephrine injection for anaphylaxis. Clostridium spores can be present on the skin and introduced into the deep tissue with subcutaneous or intramuscular injection. While cleansing with alcohol may reduce the presence of bacteria on the skin, alcohol cleansing does not kill Clostridium spores. To decrease the potential risk of a rare, but serious Clostridium infection, do not inject AUVI-Q into the buttock [see Warnings and Precautions (5.2)]. Advise patients to seek medical care if they develop signs or symptoms of infection, such as persistent redness, warmth, swelling, or tenderness, at the epinephrine injection site.

5.4 Allergic Reactions Associated with Sulfite

Epinephrine is the preferred treatment for serious allergic reactions or other emergency situations even though this product contains sodium bisulfite, a sulfite that may, in other products, cause allergic-type reactions including anaphylactic symptoms or life-threatening or less severe asthmatic episodes in certain susceptible persons.

The presence of a sulfite in this product should not deter administration of the drug for treatment of serious allergic or other emergency situations even if the patient is sulfite-sensitive.

The alternatives to using epinephrine in a life-threatening situation may not be satisfactory.

5.5 Disease Interactions

Some patients may be at greater risk for developing adverse reactions after epinephrine administration. Despite these concerns, it should be recognized that the presence of these conditions is not a contraindication to epinephrine administration in an acute, life-threatening situation. Therefore, patients with these conditions, and/or any other person who might be in a position to administer AUVI-Q to a patient experiencing anaphylaxis should be carefully instructed in regard to the circumstances under which epinephrine should be used.

Patients with Heart Disease

Epinephrine should be administered with caution to patients who have heart disease, including patients with cardiac arrhythmias, coronary artery or organic heart disease, or hypertension. In such patients, or in patients who are on drugs that may sensitize the heart to arrhythmias, epinephrine may precipitate or aggravate angina pectoris as well as produce ventricular arrhythmias [see Drug Interactions (7) and Adverse Reactions (6)].

Other Patients and Diseases

Epinephrine should be administered with caution to patients with hyperthyroidism, diabetes, elderly individuals, and pregnant women. Patients with Parkinson’s disease may notice a temporary worsening of symptoms.

6 ADVERSE REACTIONS

Due to lack of randomized, controlled clinical trials of epinephrine for the treatment of anaphylaxis, the true incidence of adverse reactions associated with the systemic use of epinephrine is difficult to determine. Adverse reactions reported in observational trials, case reports, and studies are listed below.

Common adverse reactions to systemically administered epinephrine include anxiety; apprehensiveness; restlessness; tremor; weakness; dizziness; sweating; palpitations; pallor; nausea and vomiting; headache; and/or respiratory difficulties. These symptoms occur in some persons receiving therapeutic doses of epinephrine, but are more likely to occur in patients with hypertension or hyperthyroidism [see Warnings and Precautions (5.5)].

Arrhythmias, including fatal ventricular fibrillation, have been reported, particularly in patients with underlying cardiac disease or those receiving certain drugs [see Warnings and Precautions (5.5) and Drug Interactions (7)].

Rapid rises in blood pressure have produced cerebral hemorrhage, particularly in elderly patients with cardiovascular disease [see Warnings and Precautions (5.5)].

Angina may occur in patients with coronary artery disease [see Warnings and Precautions (5.5)].

Rare cases of stress cardiomyopathy have been reported in patients treated with epinephrine.

Accidental injection into the digits, hands or feet may result in loss of blood flow to the affected area [see Warnings and Precautions (5.2)].

Adverse events experienced as a result of accidental injections may include increased heart rate, local reactions including injection site pallor, coldness and hypoesthesia or injury at the injection site resulting in bruising, bleeding, discoloration, erythema or skeletal injury.

Injection of epinephrine into the buttock has resulted in cases of gas gangrene [see Warnings and Precautions (5.2)].

Rare cases of serious skin and soft tissue infections, including necrotizing fasciitis and myonecrosis caused by Clostridia (gas gangrene), have been reported at the injection site following epinephrine injection in the thigh [see Warnings and Precautions (5.2)].

7 DRUG INTERACTIONS

7.1 Drugs Increasing Risk of Cardiac Arrhythmias

Patients who receive epinephrine while concomitantly taking cardiac glycosides, diuretics, or anti-arrhythmics should be observed carefully for the development of cardiac arrhythmias [see Warnings and Precautions (5.5)].

7.2 Drugs Potentiating Effects of Epinephrine

The effects of epinephrine may be potentiated by tricyclic antidepressants, monoamine oxidase inhibitors, levothyroxine sodium, and certain antihistamines, notably chlorpheniramine, tripelennamine, and diphenhydramine.

7.3 Drugs Antagonizing Effects of Epinephrine

The cardiostimulating and bronchodilating effects of epinephrine are antagonized by beta-adrenergic blocking drugs, such as propranolol.

The vasoconstricting and hypertensive effects of epinephrine are antagonized by alpha-adrenergic blocking drugs, such as phentolamine.

Ergot alkaloids may also reverse the pressor effects of epinephrine.

8 USE IN SPECIFIC POPULATIONS

8.1 Pregnancy

Risk Summary

There are no adequate and well controlled studies of the acute effect of epinephrine in pregnant women. In animal reproductive studies, epinephrine administered by the subcutaneous route to rabbits, mice, and hamsters during the period of organogenesis was teratogenic at doses 7 times and higher than the maximum recommended human intramuscular and subcutaneous dose on a mg/m2 basis. Epinephrine is the first-line medication of choice for the treatment of anaphylaxis during pregnancy in humans. Epinephrine should be used for treatment of anaphylaxis during pregnancy in the same manner as it is used in non-pregnant patients.

In the U.S. general population, the estimated background risk of major birth defects and miscarriage in clinically recognized pregnancies is 2 to 4% and 15 to 20%, respectively.

Clinical Considerations

Disease-associated maternal and embryo/fetal risk:

During pregnancy, anaphylaxis can be catastrophic and can lead to hypoxic-ischemic encephalopathy and permanent central nervous system damage or death in the mother and, more commonly, in the fetus or neonate. The prevalence of anaphylaxis occurring during pregnancy is reported to be approximately 3 cases per 100,000 deliveries.

Management of anaphylaxis during pregnancy is similar to management in the general population. Epinephrine is the first line-medication of choice for treatment of anaphylaxis; it should be used in the same manner in pregnant and non-pregnant patients. In conjunction with the administration of epinephrine, the patient should seek immediate medical or hospital care.

Data

Animal Data:

In an embryofetal development study with rabbits dosed during the period of organogenesis, epinephrine was shown to be teratogenic (including gastroschisis and embryonic lethality) at doses approximately 40 times the maximum recommended intramuscular or subcutaneous dose (on a mg/m2 basis at a maternal subcutaneous dose of 1.2 mg/kg/day for two to three days).

In an embryofetal development study with mice dosed during the period of organogenesis, epinephrine was shown to be teratogenic (including embryonic lethality) at doses approximately 8 times the maximum recommended intramuscular or subcutaneous dose (on a mg/m2 basis at a maternal subcutaneous dose of 1 mg/kg/day for 10 days). These effects were not seen in mice at approximately 4 times the maximum recommended daily intramuscular or subcutaneous dose (on a mg/m2 basis at a subcutaneous maternal dose of 0.5 mg/kg/day for 10 days).

In an embryofetal development study with hamsters dosed during the period of organogenesis from gestation days 7 to 10, epinephrine was shown to be teratogenic at doses approximately 7 times the maximum recommended daily intramuscular or subcutaneous dose (on a mg/m2 basis at a maternal subcutaneous dose of 0.5 mg/kg/day for 4 days).

8.2 Lactation

Risk Summary

There is no information on the presence of epinephrine in human milk, the effects on breastfed infants, or the effects on milk production. Epinephrine is the first line-medication of choice for treatment of anaphylaxis; it should be used in the same manner in breastfeeding and non-breastfeeding patients.

8.4 Pediatric Use

AUVI-Q may be administered to pediatric patients at a dosage appropriate to body weight [see Dosage and Administration (2)]. Clinical experience with the use of epinephrine suggests that the adverse reactions seen in children are similar in nature and extent to those both expected and reported in adults. Since the doses of epinephrine delivered from AUVI-Q are fixed, consider using other forms of injectable epinephrine if doses lower than 0.1 mg are deemed necessary.

8.5 Geriatric Use

Clinical studies of AUVI-Q did not include sufficient numbers of subjects aged 65 and over to determine whether they respond differently from younger subjects. Other reported clinical experience has not identified differences in responses between the elderly and younger patients. Epinephrine should be administered with caution in elderly individuals, who may be at greater risk for developing adverse reactions after epinephrine administration [see Warnings and Precautions (5.5), Overdosage (10)].

10 OVERDOSAGE

Overdosage of epinephrine may produce extremely elevated arterial pressure, which may result in cerebrovascular hemorrhage, particularly in elderly patients. Overdosage may also result in pulmonary edema because of peripheral vascular constriction together with cardiac stimulation. Treatment consists of rapidly acting vasodilators or alpha-adrenergic blocking drugs and/or respiratory support.

Epinephrine overdosage can also cause transient bradycardia followed by tachycardia, and these may be accompanied by potentially fatal cardiac arrhythmias. Premature ventricular contractions may appear within one minute after injection and may be followed by multifocal ventricular tachycardia (prefibrillation rhythm). Subsidence of the ventricular effects may be followed by atrial tachycardia and occasionally by atrioventricular block. Treatment of arrhythmias consists of administration of a beta-adrenergic blocking drug such as propranolol.

Overdosage sometimes results in extreme pallor and coldness of the skin, metabolic acidosis, and kidney failure. Suitable corrective measures must be taken in such situations.

11 DESCRIPTION

AUVI-Q (epinephrine injection, USP) 0.3 mg, 0.15 mg and 0.1 mg is an autoinjector and a combination product containing drug and device components.

AUVI-Q includes audible (electronic voice instructions, beeps) and visible (LED lights) cues for use. The needle automatically retracts after the injection is complete.

Each AUVI-Q 0.3 mg delivers a single dose of 0.3 mg epinephrine from epinephrine injection, USP (0.3 mL) in a sterile solution.

Each AUVI-Q 0.15 mg delivers a single dose of 0.15 mg epinephrine from epinephrine injection, USP (0.15 mL) in a sterile solution.

Each AUVI-Q 0.1 mg delivers a single dose of 0.1 mg epinephrine from epinephrine injection, USP (0.1 mL) in a sterile solution .

AUVI-Q 0.3 mg, AUVI-Q 0.15 mg and AUVI-Q 0.1 mg each contain 0.76 mL epinephrine solution. 0.3 mL, 0.15 mL and 0.1 mL epinephrine solution is dispensed for AUVI-Q 0.3 mg, AUVI-Q 0.15 mg and AUVI-Q 0.1 mg, respectively, when activated. The remaining solution is not available for future use and should be discarded.

Each 0.3 mL in AUVI-Q 0.3 mg contains 0.3 mg epinephrine, 2.3 mg sodium chloride, 0.5 mg sodium bisulfite, hydrochloric acid to adjust pH, and water for injection. The pH range is 2.2–5.0.

Each 0.15 mL in AUVI-Q 0.15 mg contains 0.15 mg epinephrine, 1.2 mg sodium chloride, 0.2 mg sodium bisulfite, hydrochloric acid to adjust pH, and water for injection. The pH range is 2.2–5.0.

Each 0.1 mL in AUVI-Q 0.1 mg contains 0.1 mg epinephrine, 0.78 mg sodium chloride, 0.15 mg sodium bisulfite, hydrochloric acid to adjust pH, and water for injection. The pH range is 2.2–5.0.

Epinephrine is a sympathomimetic catecholamine. Chemically, epinephrine is (-)-3,4-Dihydroxy-α-[(methylamino)methyl]benzyl alcohol with the following structure:

Epinephrine solution deteriorates rapidly on exposure to air or light, turning pink from oxidation to adrenochrome and brown from the formation of melanin.

AUVI-Q is not made with natural rubber latex.

AUVI-Q instructional and safety systems should be thoroughly reviewed with patients and caregivers prior to use [see Patient Counseling Information (17)].

12 CLINICAL PHARMACOLOGY

12.1 Mechanism of Action

Epinephrine acts on both alpha and beta-adrenergic receptors.

12.2 Pharmacodynamics

Through its action on alpha-adrenergic receptors, epinephrine lessens the vasodilation and increased vascular permeability that occurs during anaphylaxis, which can lead to loss of intravascular fluid volume and hypotension.

Through its action on beta-adrenergic receptors, epinephrine causes bronchial smooth muscle relaxation and helps alleviate bronchospasm, wheezing and dyspnea that may occur during anaphylaxis.

Epinephrine also alleviates pruritus, urticaria, and angioedema and may relieve gastrointestinal and genitourinary symptoms associated with anaphylaxis because of its relaxer effects on the smooth muscle of the stomach, intestine, uterus and urinary bladder.

When given subcutaneously or intramuscularly, epinephrine has a rapid onset and short duration of action.

13 NONCLINICAL TOXICOLOGY

13.1 Carcinogenesis, Mutagenesis, Impairment of Fertility

Long-term studies to evaluate the carcinogenic potential of epinephrine have not been conducted.

Epinephrine and other catecholamines have been shown to have mutagenic potential in vitro. Epinephrine was positive in the Salmonella bacterial reverse mutation assay, positive in the mouse lymphoma assay, and negative in the in vivo micronucleus assay. Epinephrine is an oxidative mutagen based on the E. coli WP2 Mutoxitest bacterial reverse mutation assay. This should not prevent the use of epinephrine under the conditions noted under the Indications and Usage (1).

The potential for epinephrine to impair reproductive performance has not been evaluated, but epinephrine has been shown to decrease implantation in female rabbits dosed subcutaneously with 1.2 mg/kg/day (40-fold the highest human intramuscular or subcutaneous daily dose) during gestation days 3 to 9.

16 HOW SUPPLIED

Storage and Handling

Epinephrine is light sensitive and should be stored in the outer case provided to protect it from light. Store at 20℃ to 25℃ (68℉ to 77℉); excursions permitted to 15℃ to 30℃℉ (59℉ to 86℉) [See USP Controlled Room Temperature]. Do not freeze. Before using, check to make sure the solution in the autoinjector is clear and colorless. Replace the autoinjector if the solution is discolored, cloudy, or contains particles.

17 PATIENT COUNSELING INFORMATION

Advise the patient to read the FDA-approved patient labeling (Patient Information and Instructions for Use).

A healthcare provider should review the patient instructions and operation of AUVI-Q, in detail, with the patient or caregiver.

Epinephrine is essential for the treatment of anaphylaxis. Patients who are at risk of or with a history of severe allergic reactions (anaphylaxis) to insect stings or bites, foods, drugs, and other allergens, as well as idiopathic and exercise-induced anaphylaxis, should be carefully instructed about the circumstances under which epinephrine should be used.

Administration and Training

Instruct patients and/or caregivers in the appropriate use of AUVI-Q. AUVI-Q should be injected into the middle of the outer thigh (through clothing, if necessary). Each device is a single-dose injection. Advise patients to seek immediate medical care in conjunction with administration of AUVI-Q.

Young children or infants may be uncooperative and kick or move during an injection. Instruct caregivers to hold the leg of young children or infants firmly in place and limit movement prior to and during injection [see Warnings and Precautions (5.2)].

Complete patient information, including dosage, directions for proper administration and precautions can be found inside each AUVI-Q carton. Review AUVI-Q’s instructional and safety systems with patients and/or caregivers. These systems include the printed label on the surface of AUVI-Q showing instructions for use and a diagram depicting the injection process, an automatic needle retraction system, visual prompts, electronic beeps, and voice instructions for use. Instruct patients and/or caregivers that the needle will not be visible after the injection and they may not feel the injection when it occurs. Instruct patients that AUVI-Q includes a 2-second countdown after it is activated and then the voice instructions will indicate the injection is complete and to seek emergency medical attention. Instruct patients that AUVI-Q’s black base will lock up onto the device housing and the lights will blink red after the injection is complete. These post-use indicators help patients and/or caregivers know that AUVI-Q has been activated and an epinephrine injection administered.

Instruct patients and/or caregivers to use and practice with the Trainer to familiarize themselves with the use of AUVI-Q in an allergic emergency. The Trainer may be used multiple times.

Adverse Reactions

Epinephrine may produce symptoms and signs that include an increase in heart rate, the sensation of a more forceful heartbeat, palpitations, sweating, nausea and vomiting, difficulty breathing, pallor, dizziness, weakness or shakiness, headache, apprehension, nervousness, or anxiety. These symptoms and signs usually subside rapidly, especially with rest, quiet and recumbency. Patients with hypertension or hyperthyroidism may develop more severe or persistent effects, and patients with coronary artery disease could experience angina. Patients with diabetes may develop increased blood glucose levels following epinephrine administration. Patients with Parkinson’s disease may notice a temporary worsening of symptoms [see Warnings and Precautions (5.5)].

Accidental Injection

Patients should be advised to seek immediate medical care in the case of accidental injection. Since epinephrine is a strong vasoconstrictor when injected into the digits, hands, or feet, treatment should be directed at vasodilatation if there is such an accidental injection to these areas [see Warnings and Precautions (5.2)].

Serious Infections at the Injection Site

Rare cases of serious skin and soft tissue infections, including necrotizing fasciitis and myonecrosis caused by Clostridia (gas gangrene), have been reported at the injection site following epinephrine injection for anaphylaxis. Advise patients to seek medical care if they develop signs or symptoms of infection, such as persistent redness, warmth, swelling, or tenderness, at the epinephrine injection site [see Warnings and Precautions (5.3)].

Storage and Handling

Patients should be instructed to inspect the epinephrine solution visually through the viewing window periodically. AUVI-Q should be replaced if the epinephrine solution appears discolored (pinkish color or darker than slightly yellow), cloudy, or contains particles. Epinephrine is light sensitive and should be stored in the outer case provided to protect it from light. Instruct patients that AUVI-Q must be used or properly disposed once the red safety guard is removed [see How Supplied/ Storage and Handling (16)].

Complete patient information, including dosage, directions for proper administration and precautions can be found inside each AUVI-Q carton.